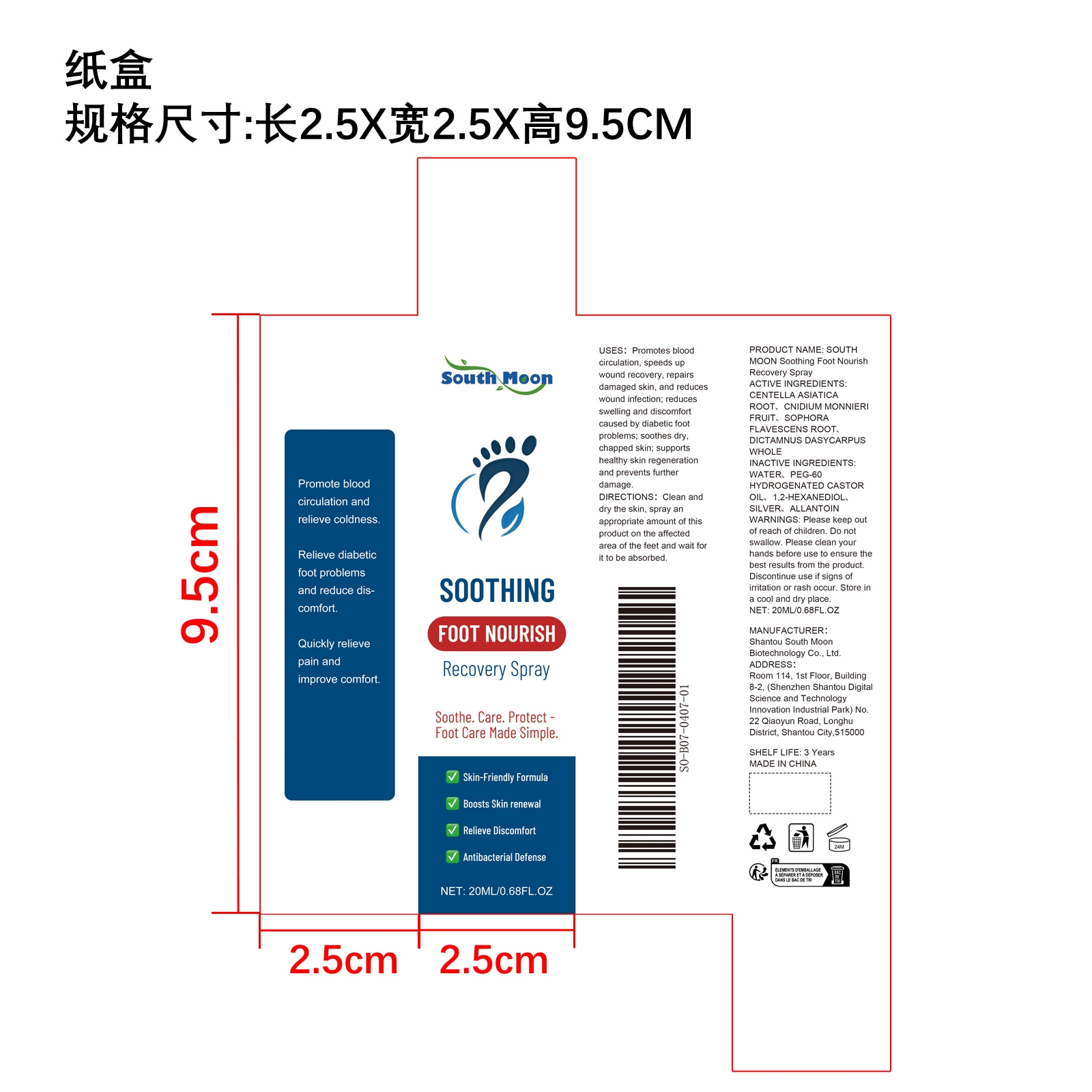 DRUG LABEL: SOUTH MOON Soothing Foot Nourish Recovery
NDC: 84983-015 | Form: LIQUID
Manufacturer: Shantou South Moon Biotechnology Co., Ltd.
Category: otc | Type: HUMAN OTC DRUG LABEL
Date: 20251127

ACTIVE INGREDIENTS: CNIDIUM MONNIERI FRUIT 0.004 mg/20 mg; DICTAMNUS DASYCARPUS WHOLE 0.004 mg/20 mg; CENTELLA ASIATICA ROOT 0.04 mg/20 mg; SOPHORA FLAVESCENS ROOT 0.004 mg/20 mg
INACTIVE INGREDIENTS: 1,2-HEXANEDIOL 0.1 mg/20 mg; SILVER 0.04 mg/20 mg; PEG-60 HYDROGENATED CASTOR OIL 0.12 mg/20 mg; ALLANTOIN 0.004 mg/20 mg; WATER 19.684 mg/20 mg

ACTIVE INGREDIENT

CENTELLA ASIATICA ROOT、CNIDIUM MONNIERI FRUIT、SOPHORA FLAVESCENS ROOT、DICTAMNUS DASYCARPUS WHOLECENTELLA ASIATICA ROOT

PURPOSE

1. Relieve foot discomfort, comfortable and refreshing.

2. Improve blood circulation and relax muscles.

3. Deeply repair and revitalize the feet.

4. Long-lasting moisturizing, nourishing feet, comfortable and natural.

WHEN USING

Clean and dry the skin, spray an appropriate amount of this product on the affected area of the feet and wait for it to be absorbed.

WARNINGS

Please keep out of reach of children. Do not swallow.Please clean your hands before use to ensure the best results from the product. Discontinue use if signs of irritation or rash occur. Store in a cool and dry place.

DO NOT USE

Discontinue use if signs of irritation or rash occur.

STOP USE

Discontinue use if signs of irritation or rash occur.

KEEP OUT OF REACH OF CHILDREN

Please keep out of reach of children. Do not swallow.

STORAGE AND HANDLING

Store in a cool and dry place.

INACTIVE INGREDIENT

WATER、PEG-60 HYDROGENATED CASTOR OIL、1,2-HEXANEDIOL、SILVER、ALLANTOIN

DOSAGE AND ADMINISTRATION

Clean and dry the skin, spray an appropriate amount of this product on the affected area of the feet and wait for it to be absorbed.

INDICATIONS AND USAGE

Clean and dry the skin, spray an appropriate amount of this product on the affected area of the feet and wait for it to be absorbed.